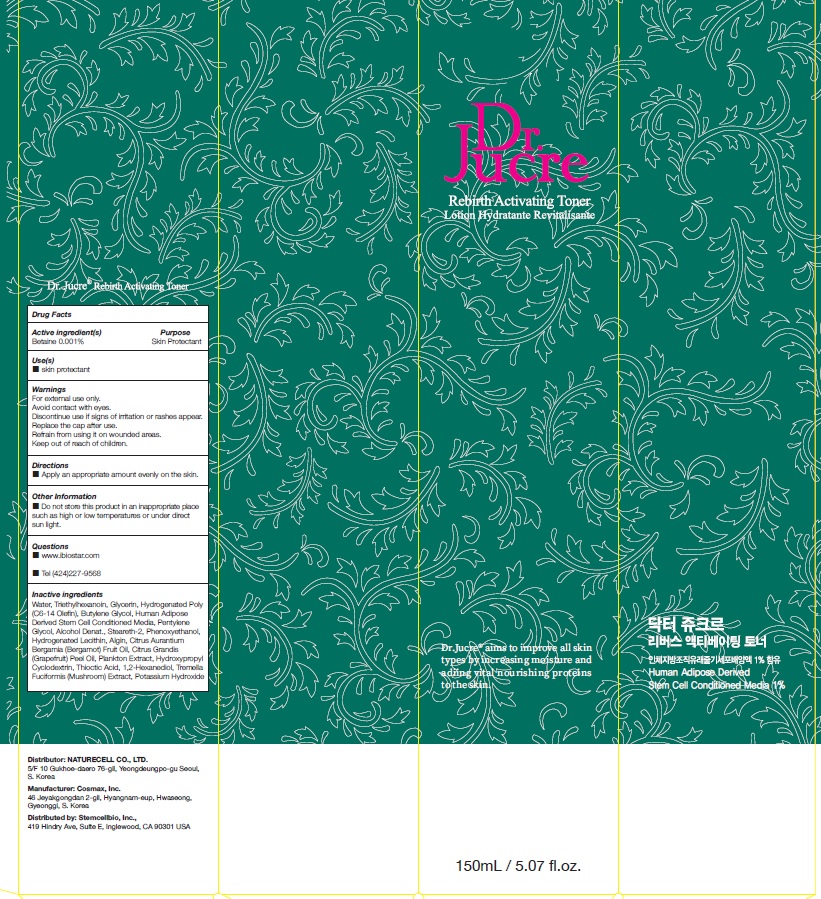 DRUG LABEL: Dr.Jucre Rebirth Activating Toner
NDC: 83071-020 | Form: LIQUID
Manufacturer: NATURECELL CO., LTD.
Category: otc | Type: HUMAN OTC DRUG LABEL
Date: 20221107

ACTIVE INGREDIENTS: Betaine 0.001 g/100 mL
INACTIVE INGREDIENTS: Water; Triethylhexanoin; Glycerin

ACTIVE INGREDIENTS

Betaine 0.001%

INACTIVE INGREDIENTS

Water, Triethylhexanoin, Glycerin, Hydrogenated Poly(C6-14 Olefin), Butylene Glycol, Human Adipose Derived Stem Cell Conditioned Media, Pentylene Glycol, Alcohol Denat., Steareth-2, Phenoxyethanol, Hydrogenated Lecithin, Algin, Citrus Aurantium Bergamia (Bergamot) Fruit Oil, Citrus Grandis (Grapefruit) Peel Oil, Plankton Extract, Hydroxypropyl Cyclodextrin, Thioctic Acid, 1,2-Hexanediol, Tremella Fuciformis (Mushroom) Extract, Potassium Hydroxide

PURPOSE

Skin Protectant

WARNINGS

For external use only.
Avoid contact with eyes.
Discontinue use if signs of irritation or rashes appear.
Replace the cap after use.
Refrain from using it on wounded areas.
Keep out of reach of children.

KEEP OUT OF REACH OF CHILDREN

Keep out of the reach of children.

Uses

■ skin protectant

Directions

■ Apply an appropriate amount evenly on the skin.

Other Information

■ Do not store this product in an inappropriate place such as high or low temperatures or under direct sun light.

Questions

■ www.ibiostar.com
■ Tel (424)227-9568